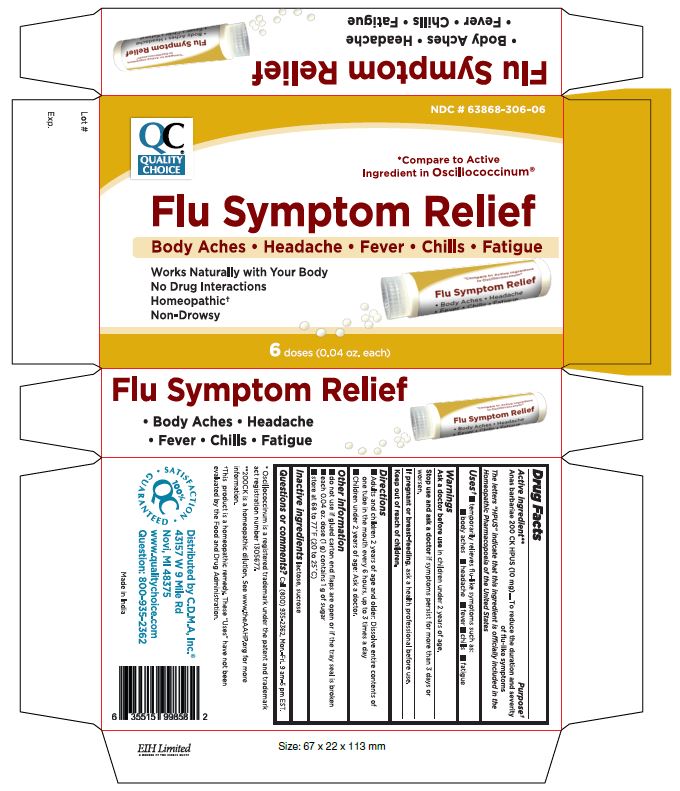 DRUG LABEL: CAIRINA MOSCHATA HEART/LIVER AUTOLYSATE
NDC: 63868-306 | Form: PELLET
Manufacturer: CHAIN DRUG MARKETING ASSOCIATION INC.
Category: homeopathic | Type: HUMAN OTC DRUG LABEL
Date: 20241227

ACTIVE INGREDIENTS: CAIRINA MOSCHATA HEART/LIVER AUTOLYSATE 200 [hp_C]/1 1
INACTIVE INGREDIENTS: LACTOSE, UNSPECIFIED FORM; SUCROSE

QC Flu Symptom Relief

Active Ingredient Purpose

Anas barbariae 200 CK HPUS ............. To reduce the duration and severity of flu-like symptoms

The letters "HPUS" indicate that this ingredient is officially included in the Homeopathic Pharmacopoeia of the United States

USES

INDICATIONS AND USAGE

- Temporarily relieves ﬂu-like symptoms such as:
  - Body aches
  - Headache
  - Fever
  - Chills
  - Fatigue

WARNINGS

Warnings
Ask a doctor before use in children under 2 years of age.

Stop use and ask a doctor if symptoms persist for more than 3 days or worsen.

If pregnant or breast-feeding, ask a health professional before use.

Keep out of reach of children.

Directions

Adults and children 2 years of age and older:

- Dissolve entire contents of one tube in the mouth every 6 hours, up to 3 times a day
- Children under 2 years of age: Ask a doctor.

Other information

- do not use if glued carton end flaps are open or if the tray seal is broken.
- each 0.04 oz. dose (1g) contains 1 g of sugar
- store at 68˚F to 77˚F (20˚C to 25˚C)

Questions or comments?
Call (800) 935-2362, Mon.-Fri. 9 am-5 pm EST.

Distributed by: C.D.M.A.Inc.
43157 W 9 Mile Rd
Novi, MI 48375
www.qualitychoice.com

Inactive ingredients

lactose, sucrose

- Compared to active ingredient in Oscillococcinum
- Oscillococcinum is a registered trademark under the patent and trademark act registration number 1305677.
- 200CK is a homeopathic dilution. See www.theAAHP.org for more information.
- This product is a homeopathic remedy. These “Uses” have not been evaluated by the Food and Drug Administration.